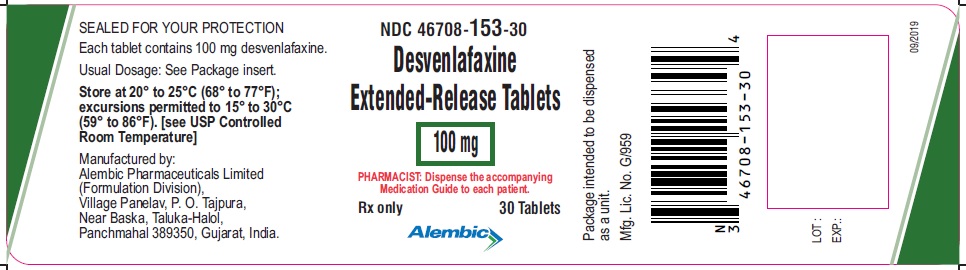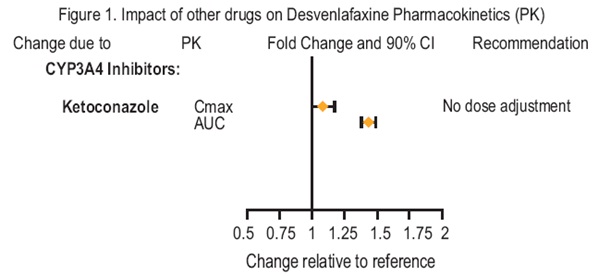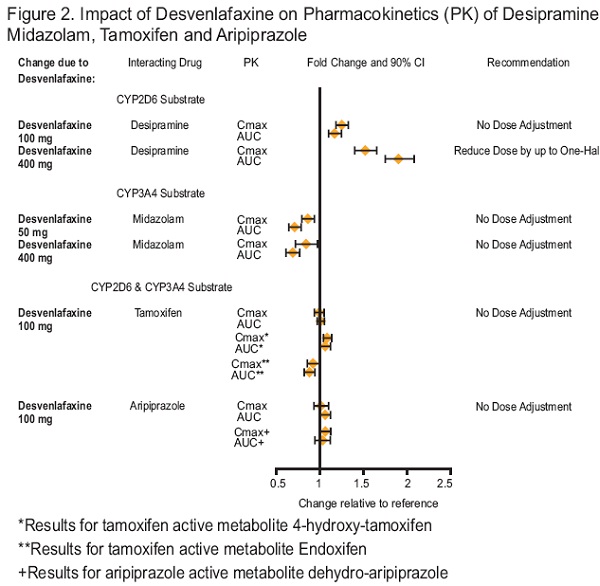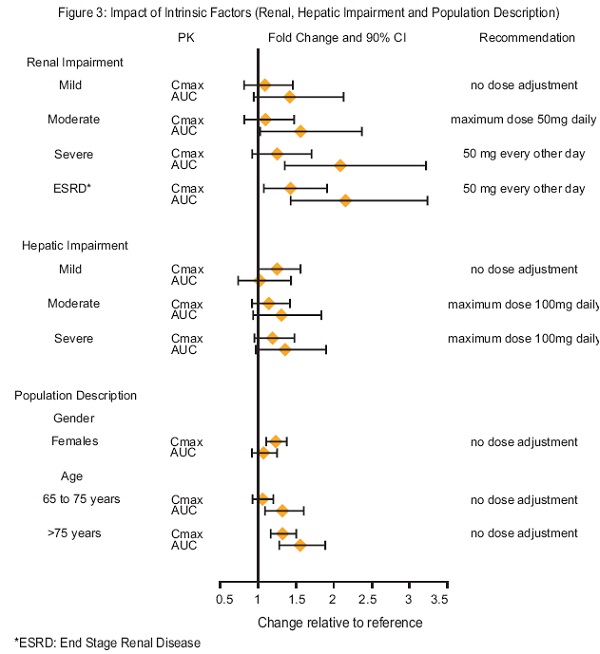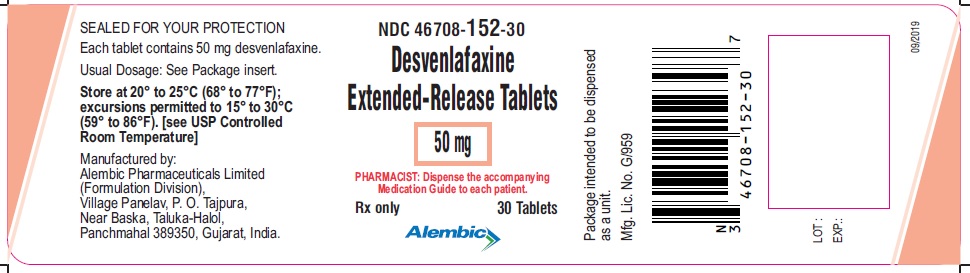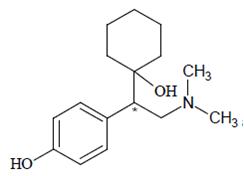 DRUG LABEL: Desvenlafaxine
NDC: 46708-152 | Form: TABLET, EXTENDED RELEASE
Manufacturer: Alembic Pharmaceuticals Limited
Category: prescription | Type: Human Prescription Drug Label
Date: 20230127

ACTIVE INGREDIENTS: DESVENLAFAXINE 50 mg/1 1
INACTIVE INGREDIENTS: ALGINIC ACID; CITRIC ACID MONOHYDRATE; HYPROMELLOSE, UNSPECIFIED; MICROCRYSTALLINE CELLULOSE; POVIDONE K30; TALC; MAGNESIUM STEARATE; TITANIUM DIOXIDE; POLYETHYLENE GLYCOL 6000; FERRIC OXIDE RED

HIGHLIGHTS OF PRESCRIBING INFORMATION

These highlights do not include all the information needed to use DESVENLAFAXINE safely and effectively. See full prescribing information for DESVENLAFAXINE.
DESVENLAFAXINE extended-release tablets, for oral use
Initial U.S. Approval: 2008

RECENT MAJOR CHANGES

Warnings and Precautions – Serotonin Syndrome (5.2) 1/2017

WARNING: SUICIDAL THOUGHTS AND BEHAVIORS

See full prescribing information for complete boxed warning.

- Increased risk of suicidal thinking and behavior in children, adolescents and young adults taking antidepressants (5.1).
- Monitor for worsening and emergence of suicidal thoughts and behaviors (5.1)
- Desvenlafaxine is not approved for use in pediatric patients (8.4).

1 INDICATIONS AND USAGE

Desvenlafaxine is a serotonin and norepinephrine reuptake inhibitor (SNRI) indicated for the treatment of major depressive disorder (MDD) (1).

2 DOSAGE AND ADMINISTRATION

- Recommended dose: 50 mg once daily with or without food (2.1).
- There was no evidence that doses greater than 50 mg per day confer any additional benefit (2.1).
- Discontinuation: Reduce dose gradually whenever possible (2.1).
- Take tablets whole; do not divide, crush, chew, or dissolve (2.1).
- Moderate renal impairment: Maximum dose 50 mg per day (2.2).
- Severe renal impairment and end-stage renal disease: Maximum dose 50 mg every other day (2.2).
- Moderate to severe hepatic impairment: Maximum dose 100 mg per day (2.2).

3 DOSAGE FORMS AND STRENGTHS

Desvenlafaxine extended-release tablets are available as 50 and 100 mg tablets (3)

4 CONTRAINDICATIONS

- Hypersensitivity to desvenlafaxine succinate, venlafaxine hydrochloride or any excipients in the desvenlafaxine extended-release tablets formulation (4).
- Serotonin syndrome and MAOIs: Do not use MAOIs intended to treat psychiatric disorders with desvenlafaxine or within 7 days of stopping treatment with desvenlafaxine. Do not use desvenlafaxine within 14 days of stopping an MAOI intended to treat psychiatric disorders. In addition, do not start desvenlafaxine in a patient who is being treated with linezolid or intravenous methylene blue (4).

5 WARNINGS AND PRECAUTIONS

- Clinical Worsening/Suicide Risk: Monitor for clinical worsening and suicide risk (5.1).
- Serotonin Syndrome: Serotonin syndrome has been reported with SSRIs and SNRIs, including with desvenlafaxine extended-release tablets, both when taken alone, but especially when co-administered with other serotonergic agents (including triptans, tricyclic antidepressants, fentanyl, lithium, tramadol, tryptophan, buspirone, amphetamines, and St. John's Wort). If such symptoms occur, discontinue desvenlafaxine and initiate supportive treatment. If concomitant use of desvenlafaxine with other serotonergic drugs is clinically warranted, patients should be made aware of a potential increased risk for serotonin syndrome, particularly during treatment initiation and dose increases (5.2).
- Elevated Blood Pressure: Controlhypertension before initiating treatment. Monitor blood pressure regularly during treatment (5.3).
- Abnormal Bleeding: Desvenlafaxine may increase risk of bleeding events. Caution patients about risk of bleeding associated with concomitant use of desvenlafaxine and NSAIDs, aspirin, or other drugs that affect coagulation (5.4).
- Angle Closure Glaucoma: Angle closure glaucoma has occurred in patients with untreated anatomically narrow angles treated with antidepressants (5.5)
- Activation of Mania/Hypomania: Use cautiously in patients with Bipolar Disorder. Caution patients about risk of activation of mania/hypomania (5.6).
- Discontinuation Syndrome: Taper dose when possible and monitor for discontinuation symptoms (5.7).
  - Seizure: Can occur. Use cautiously in patients with seizure disorder (5.8).
- Hyponatremia: Can occur in association with SIADH (5.9).
- Interstitial Lung Disease and Eosinophilic Pneumonia: Can occur (5.10).

6 ADVERSE REACTIONS

Most common adverse reactions (incidence ≥5% and twice the rate of placebo in the 50 or 100 mg dose groups) were: nausea, dizziness, insomnia, hyperhidrosis, constipation, somnolence, decreased appetite, anxiety, and specific male sexual function disorders (6.1).

To report SUSPECTED ADVERSE REACTIONS, contact FDA at 1-800-FDA-1088 or www.fda.gov/medwatch

8 USE IN SPECIFIC POPULATIONS

- Pregnancy: Based on animal data, may cause fetal harm (8.1).
- Nursing Mothers: Discontinue drug or nursing taking into consideration importance of drug to mother (8.3).
  - Geriatric Use: There is an increased incidence of orthostatic hypotension in desvenlafaxine treated patients ≥ 65 years (6.1 and 8.5).

FULL PRESCRIBING INFORMATION

WARNING: SUICIDAL THOUGHTS AND BEHAVIORS

Antidepressants increased the risk of suicidal thoughts and behavior in children, adolescents, and young adults in short-term studies. These studies did not show an increase in the risk of suicidal thoughts and behavior with antidepressant use in patients over age 24; there was a reduction in risk with antidepressant use in patients aged 65 and older [see Warnings and Precautions (5.1)].

In patients of all ages who are started on antidepressant therapy, monitor closely for worsening, and for emergence of suicidal thoughts and behaviors. Advise families and caregivers of the need for close observation and communication with the prescriber [see Warnings and Precautions (5.1)].

Desvenlafaxine is not approved for use in pediatric patients [see Use in Specific Populations (8.4)].

1 INDICATIONS AND USAGE

Desvenlafaxine, a serotonin and norepinephrine reuptake inhibitor (SNRI), is indicated for the treatment of major depressive disorder (MDD) [see Clinical Studies (14) and Dosage and Administration (2.1)]. The efficacy of desvenlafaxine has been established in four short-term (8-week, placebo-controlled studies) of outpatients who met DSM-IV criteria for major depressive disorder.

2 DOSAGE AND ADMINISTRATION

2.1 General Instruction for Use

The recommended dose for desvenlafaxine is 50 mg once daily, with or without food. The 50 mg dose is both a starting dose and the therapeutic dose. Desvenlafaxine should be taken at approximately the same time each day. Tablets must be swallowed whole with fluid and not divided, crushed, chewed, or dissolved.

In clinical studies, doses of 10 mg to 400 mg per day were studied. In clinical studies, doses of 50 mg to 400 mg per day were shown to be effective, although no additional benefit was demonstrated at doses greater than 50 mg per day and adverse reactions and discontinuations were more frequent at higher doses.

When discontinuing therapy, gradual dose reduction is recommended whenever possible to minimize discontinuation symptoms [see Dosage and Administration (2.4) and Warnings and Precautions (5.9)].

2.2 Special Populations

Patients with renal impairment

The maximum recommended dose in patients with moderate renal impairment (24-hr creatinine clearance [CrCl] = 30 to 50 mL/min, Cockcroft-Gault [C-G]) is 50 mg per day. The maximum recommended dose in patients with severe renal impairment (24-hr CrCl less than 30 mL/min, C-G) or end-stage renal disease (ESRD) is 50 mg every other day. Supplemental doses should not be given to patients after dialysis [see Use in Specific Populations (8.6) and Clinical Pharmacology (12.3)].

Patients with hepatic impairment

The recommended dose in patients with moderate to severe hepatic impairment is 50 mg per day. Dose escalation above 100 mg per day is not recommended [see Clinical Pharmacology (12.3)].

2.3 Maintenance/Continuation/Extended Treatment

It is generally agreed that acute episodes of major depressive disorder require several months or longer of sustained pharmacologic therapy. Patients should be periodically reassessed to determine the need for continued treatment.

2.4 Discontinuing Desvenlafaxine

Symptoms associated with discontinuation of desvenlafaxine, other SNRIs and SSRIs have been reported [see Warnings and Precautions (5.9)]. Patients should be monitored for these symptoms when discontinuing treatment. A gradual reduction in the dose rather than abrupt cessation is recommended whenever possible. If intolerable symptoms occur following a decrease in the dose or upon discontinuation of treatment, then resuming the previously prescribed dose may be considered. Subsequently, the physician may continue decreasing the dose, but at a more gradual rate.

2.5 Switching Patients From Other Antidepressants to Desvenlafaxine

Discontinuation symptoms have been reported when switching patients from other antidepressants, including venlafaxine, to desvenlafaxine. Tapering of the initial antidepressant may be necessary to minimize discontinuation symptoms.

2.6 Switching Patients To or From a Monoamine Oxidase Inhibitor (MAOI) Intended to Treat Psychiatric Disorders

At least 14 days should elapse between discontinuation of an MAOI intended to treat psychiatric disordersand initiation of therapy with desvenlafaxine. Conversely, at least 7 days should be allowed after stopping desvenlafaxine before starting an MAOI intended to treat psychiatric disorders [see Contraindications (4)].

Use of Desvenlafaxine with other MAOIs such as Linezolid or Methylene Blue

Do not start desvenlafaxine in a patient who is being treated with linezolid or intravenous methylene blue because there is increased risk of serotonin syndrome. In a patient who requires more urgent treatment of a psychiatric condition, other interventions, including hospitalization, should be considered [see Contraindications (4)].

In some cases, a patient already receiving desvenlafaxine therapy may require urgent treatment with linezolid or intravenous methylene blue. If acceptable alternatives to linezolid or intravenous methylene blue treatment are not available and the potential benefits of linezolid or intravenous methylene blue treatment are judged to outweigh the risks of serotonin syndrome in a particular patient, desvenlafaxine should be stopped promptly, and linezolid or intravenous methylene blue can be administered. The patient should be monitored for symptoms of serotonin syndrome for 7 days or until 24 hours after the last dose of linezolid or intravenous methylene blue, whichever comes first. Therapy with desvenlafaxine may be resumed 24 hours after the last dose of linezolid or intravenous methylene blue [see Warnings and Precautions (5.2)].

The risk of administering methylene blue by non-intravenous routes (such as oral tablets or by local injection) or in intravenous doses much lower than 1 mg/kg with desvenlafaxine is unclear. The clinician should, nevertheless, be aware of the possibility of emergent symptoms of serotonin syndrome with such use [see Warnings and Precautions (5.2)].

3 DOSAGE FORMS AND STRENGTHS

Desvenlafaxine extended-release tablets are available as 50 and 100 mg tablets.

- 50 mg, light pink colored, diamond shaped, biconvex tablets, debossed with ‘L189’ on one side and plain on other side.

- 100 mg, dark brown to red colored, diamond shaped, biconvex tablets, debossed with ‘L190’ on one side and plain on other side.

4 CONTRAINDICATIONS

- Hypersensitivity to desvenlafaxine succinate, venlafaxine hydrochloride or to any excipients in the desvenlafaxine extended-release tablets formulation. Angioedema has been reported in patients treated with desvenlafaxine [see Adverse Reactions (6.1)].
- The use of MAOIs intended to treat psychiatric disorders with desvenlafaxine or within 7 days of stopping treatment with desvenlafaxine is contraindicated because of an increased risk of serotonin syndrome. The use of desvenlafaxine within 14 days of stopping an MAOI intended to treat psychiatric disorders is also contraindicated [see Dosage and Administration (2.6) and Warnings and Precautions (5.2)].
- Starting desvenlafaxine in a patient who is being treated with MAOIs such as linezolid or intravenous methylene blue is also contraindicated because of an increased risk of serotonin syndrome [see Dosage and Administration (2.6) and Warnings and Precautions (5.2)].

5 WARNINGS AND PRECAUTIONS

5.1 Suicidal Thoughts and Behaviors in Children, Adolescents and Young Adults

Patients with major depressive disorder (MDD), both adult and pediatric, may experience worsening of their depression and/or the emergence of suicidal ideation and behavior (suicidality) or unusual changes in behavior, whether or not they are taking antidepressant medications, and this risk may persist until significant remission occurs. Suicide is a known risk of depression and certain other psychiatric disorders, and these disorders themselves are the strongest predictors of suicide. There has been a long-standing concern, however, that antidepressants may have a role in inducing worsening of depression and the emergence of suicidality in certain patients during the early phases of treatment. Pooled analyses of short-term placebo-controlled studies of antidepressant drugs (SSRIs and others) showed that these drugs increase the risk of suicidal thinking and behavior (suicidality) in children, adolescents, and young adults (ages 18 to 24) with major depressive disorder (MDD) and other psychiatric disorders. Short-term studies did not show an increase in the risk of suicidality with antidepressants compared to placebo in adults beyond age 24; there was a reduction with antidepressants compared to placebo in adults aged 65 and older.

The pooled analyses of placebo-controlled studies in children and adolescents with MDD, obsessive compulsive disorder (OCD), or other psychiatric disorders included a total of 24 short-term studies of 9 antidepressant drugs in over 4,400 patients. The pooled analyses of placebo-controlled studies in adults with MDD or other psychiatric disorders included a total of 295 short-term studies (median duration of 2 months) of 11 antidepressant drugs in over 77,000 patients. There was considerable variation in risk of suicidality among drugs, but a tendency toward an increase in the younger patients for almost all drugs studied. There were differences in absolute risk of suicidality across the different indications, with the highest incidence in MDD. The risk differences (drug vs. placebo), however, were relatively stable within age strata and across indications. These risk differences (drug-placebo difference in the number of cases of suicidality per 1,000 patients treated) are provided in Table 1.

Table 1

Age Range | Drug-Placebo Difference in Number of Cases of Suicidality per 1,000 Patients Treated
 | Increases Compared to Placebo
<18 | 14 additional cases
18 to 24 | 5 additional cases
 | Decreases Compared to Placebo
25 to 64 | 1 fewer case
≥65 | 6 fewer cases

No suicides occurred in any of the pediatric studies. There were suicides in the adult studies, but the number was not sufficient to reach any conclusion about drug effect on suicide.

It is unknown whether the suicidality risk extends to longer-term use, i.e., beyond several months. However, there is substantial evidence from placebo-controlled maintenance studies in adults with depression that the use of antidepressants can delay the recurrence of depression.

All patients being treated with antidepressants for any indication should be monitored appropriately and observed closely for clinical worsening, suicidality, and unusual changes in behavior, especially during the initial few months of a course of drug therapy, or at times of dose changes, either increases or decreases.

The following symptoms, anxiety, agitation, panic attacks, insomnia, irritability, hostility, aggressiveness, impulsivity, akathisia (psychomotor restlessness), hypomania, and mania, have been reported in adult and pediatric patients being treated with antidepressants for major depressive disorder as well as for other indications, both psychiatric and nonpsychiatric. Although a causal link between the emergence of such symptoms and either the worsening of depression and/or the emergence of suicidal impulses has not been established, there is concern that such symptoms may represent precursors to emerging suicidality.

Consideration should be given to changing the therapeutic regimen, including possibly discontinuing the medication, in patients whose depression is persistently worse, or who are experiencing emergent suicidality or symptoms that might be precursors to worsening depression or suicidality, especially if these symptoms are severe, abrupt in onset, or were not part of the patient’s presenting symptoms.

If the decision has been made to discontinue treatment, medication should be tapered, as rapidly as is feasible, but with recognition that abrupt discontinuation can be associated with certain symptoms [see Dosage and Administration (2.4) and Warnings and Precautions (5.7) for a description of the risks of discontinuation of desvenlafaxine].

Families and caregivers of patients being treated with antidepressants for major depressive disorder or other indications, both psychiatric and nonpsychiatric, should be alerted about the need to monitor patients for the emergence of agitation, irritability, unusual changes in behavior, and the other symptoms described above, as well as the emergence of suicidality, and to report such symptoms immediately to healthcare providers. Such monitoring should include daily observation by families and caregivers.

Prescriptions for desvenlafaxine should be written for the smallest quantity of tablets consistent with good patient management, in order to reduce the risk of overdose.

Screening patients for bipolar disorder

A major depressive episode may be the initial presentation of bipolar disorder. It is generally believed (though not established in controlled studies) that treating such an episode with an antidepressant alone may increase the likelihood of precipitation of a mixed/manic episode in patients at risk for bipolar disorder. Whether any of the symptoms described above represent such a conversion is unknown. However, prior to initiating treatment with an antidepressant, patients with depressive symptoms should be adequately screened to determine if they are at risk for bipolar disorder; such screening should include a detailed psychiatric history, including a family history of suicide, bipolar disorder, and depression. It should be noted that desvenlafaxine is not approved for use in treating bipolar depression.

5.2 Serotonin Syndrome

The development of a potentially life-threatening serotonin syndrome has been reported with SNRIs and SSRIs, including desvenlafaxine, alone but particularly with concomitant use of other serotonergic drugs (including triptans, tricyclic antidepressants, fentanyl, lithium, tramadol, tryptophan, buspirone, amphetamines, and St. John's Wort), and with drugs that impair metabolism of serotonin (in particular, MAOIs, both those intended to treat psychiatric disorders and also others, such as linezolid and intravenous methylene blue).

Serotonin syndrome symptoms may include mental status changes (e.g., agitation, hallucinations, delirium, and coma), autonomic instability (e.g., tachycardia, labile blood pressure, dizziness, diaphoresis, flushing, hyperthermia), neuromuscular symptoms (e.g., tremor, rigidity, myoclonus, hyperreflexia, incoordination), seizures, and/or gastrointestinal symptoms (e.g., nausea, vomiting, diarrhea). Patients should be monitored for the emergence of serotonin syndrome.

The concomitant use of desvenlafaxine with MAOIs intended to treat psychiatric disorders is contraindicated. Desvenlafaxine should also not be started in a patient who is being treated with MAOIs such as linezolid or intravenous methylene blue. All reports with methylene blue that provided information on the route of administration involved intravenous administration in the dose range of 1 mg/kg to 8 mg/kg. No reports involved the administration of methylene blue by other routes (such as oral tablets or local tissue injection) or at lower doses. There may be circumstances when it is necessary to initiate treatment with a MAOI such as linezolid or intravenous methylene blue in a patient taking desvenlafaxine. Desvenlafaxine should be discontinued before initiating treatment with the MAOI [see Contraindications (4) and Dosage and Administration (2.6)].

If concomitant use of desvenlafaxine with other serotonergic drugs, including triptans, tricyclic antidepressants, fentanyl, lithium, tramadol, buspirone, amphetamines, tryptophan, and St. John's Wort is clinically warranted, patients should be made aware of a potential increased risk for serotonin syndrome, particularly during treatment initiation and dose increases.

Treatment with desvenlafaxine and any concomitant serotonergic agents should be discontinued immediately if the above events occur and supportive symptomatic treatment should be initiated.

5.3 Elevated Blood Pressure

Patients receiving desvenlafaxine should have regular monitoring of blood pressure since increases in blood pressure were observed in clinical studies [see Adverse Reactions (6.1)]. Pre-existing hypertension should be controlled before initiating treatment with desvenlafaxine. Caution should be exercised in treating patients with pre-existing hypertension, cardiovascular, or cerebrovascular conditions that might be compromised by increases in blood pressure. Cases of elevated blood pressure requiring immediate treatment have been reported with desvenlafaxine.

Sustained blood pressure increases could have adverse consequences. For patients who experience a sustained increase in blood pressure while receiving desvenlafaxine, either dose reduction or discontinuation should be considered [see Adverse Reactions (6.1)].

5.4 Abnormal Bleeding

SSRIs and SNRIs, including desvenlafaxine, may increase the risk of bleeding events. Concomitant use of aspirin, nonsteroidal anti-inflammatory drugs, warfarin, and other anticoagulants may add to this risk. Case reports and epidemiological studies (case-control and cohort design) have demonstrated an association between use of drugs that interfere with serotonin reuptake and the occurrence of gastrointestinal bleeding. Bleeding events related to SSRIs and SNRIs have ranged from ecchymosis, hematoma, epistaxis, and petechiae to life-threatening hemorrhages. Patients should be cautioned about the risk of bleeding associated with the concomitant use of desvenlafaxine and NSAIDs, aspirin, or other drugs that affect coagulation or bleeding.

5.5 Angle Closure Glaucoma

Angle-Closure Glaucoma: The pupillary dilation that occurs following use of many antidepressant drugs including desvenlafaxine may trigger an angle closure attack in a patient with anatomically narrow angles who does not have a patent iridectomy.

5.6 Activation of Mania/Hypomania

During all MDD phase 2 and phase 3 studies, mania was reported for approximately 0.02% of patients treated with desvenlafaxine. Activation of mania/hypomania has also been reported in a small proportion of patients with major affective disorder who were treated with other marketed antidepressants. As with all antidepressants, desvenlafaxine should be used cautiously in patients with a history or family history of mania or hypomania.

5.7 Discontinuation Syndrome

Discontinuation symptoms have been systematically and prospectively evaluated in patients treated with desvenlafaxine during clinical studies in Major Depressive Disorder. Abrupt discontinuation or dose reduction has been associated with the appearance of new symptoms that include dizziness, nausea, headache, irritability, insomnia, diarrhea, anxiety, fatigue, abnormal dreams, and hyperhidrosis. In general, discontinuation events occurred more frequently with longer duration of therapy.

During marketing of SNRIs (Serotonin and Norepinephrine Reuptake Inhibitors), and SSRIs (Selective Serotonin Reuptake Inhibitors), there have been spontaneous reports of adverse events occurring upon discontinuation of these drugs, particularly when abrupt, including the following: dysphoric mood, irritability, agitation, dizziness, sensory disturbances (e.g., paresthesia, such as electric shock sensations), anxiety, confusion, headache, lethargy, emotional lability, insomnia, hypomania, tinnitus, and seizures. While these events are generally self-limiting, there have been reports of serious discontinuation symptoms.

Patients should be monitored for these symptoms when discontinuing treatment with desvenlafaxine. A gradual reduction in the dose rather than abrupt cessation is recommended whenever possible. If intolerable symptoms occur following a decrease in the dose or upon discontinuation of treatment, then resuming the previously prescribed dose may be considered. Subsequently, the physician may continue decreasing the dose, but at a more gradual rate [see Dosage and Administration (2.4) and Adverse Reactions (6.1)].

5.8 Seizure

Cases of seizure have been reported in pre-marketing clinical studies with desvenlafaxine. Desvenlafaxine has not been systematically evaluated in patients with a seizure disorder. Patients with a history of seizures were excluded from pre-marketing clinical studies. Desvenlafaxine should be prescribed with caution in patients with a seizure disorder.

5.9 Hyponatremia

Hyponatremia may occur as a result of treatment with SSRIs and SNRIs, including desvenlafaxine. In many cases, this hyponatremia appears to be the result of the syndrome of inappropriate antidiuretic hormone secretion (SIADH). Cases with serum sodium lower than 110 mmol/L have been reported. Elderly patients may be at greater risk of developing hyponatremia with SSRIs and SNRIs. Also, patients taking diuretics or who are otherwise volume depleted can be at greater risk [see Use in Specific Populations (8.5) and Clinical Pharmacology (12.6)]. Discontinuation of desvenlafaxine should be considered in patients with symptomatic hyponatremia and appropriate medical intervention should be instituted.

Signs and symptoms of hyponatremia include headache, difficulty concentrating, memory impairment, confusion, weakness, and unsteadiness, which can lead to falls. Signs and symptoms associated with more severe and/or acute cases have included hallucination, syncope, seizure, coma, respiratory arrest, and death.

5.10 Interstitial Lung Disease and Eosinophilic Pneumonia

Interstitial lung disease and eosinophilic pneumonia associated with venlafaxine (the parent drug of desvenlafaxine) therapy have been rarely reported. The possibility of these adverse events should be considered in patients treated with desvenlafaxine who present with progressive dyspnea, cough, or chest discomfort. Such patients should undergo a prompt medical evaluation, and discontinuation of desvenlafaxine should be considered.

6 ADVERSE REACTIONS

The following adverse reactions are discussed in greater detail in other sections of the label.

- Hypersensitivity [see Contraindications (4)]
- Suicidal Thoughts and Behaviors in Adolescents and Young Adults [see Warnings and Precautions (5.1)]
- Serotonin Syndrome [see Warnings and Precautions (5.2)]
- Elevated Blood Pressure [see Warnings and Precautions (5.3)]
- Abnormal Bleeding [see Warnings and Precautions (5.4)]
- Angle Closure Glaucoma [see Warnings and Precautions (5.5)]
- Activation of Mania/Hypomania [see Warnings and Precautions (5.6)]
- Discontinuation Syndrome [see Warnings and Precautions (5.7)]
- Seizure [see Warnings and Precautions (5.8)]
- Hyponatremia [see Warnings and Precautions (5.9)]
- Interstitial Lung Disease and Eosinophilic Pneumonia [see Warnings and Precautions 5.10)]

6.1 Clinical Studies Experience

Because clinical trials are conducted under widely varying conditions, adverse reaction rates observed in the clinical trials of a drug cannot be directly compared to rates in the clinical studies of another drug and may not reflect the rates observed in clinical practice.

Patient exposure

Desvenlafaxine was evaluated for safety in 8,394 patients diagnosed with major depressive disorder who participated in multiple-dose pre-marketing studies, representing 2,784 patient-years of exposure. Of the total 8,394 patients exposed to at least one dose of desvenlafaxine; 2,116 were exposed to desvenlafaxine for 6 months, representing 1,658 patient-years of exposure, and 421 were exposed for one year, representing 416 patient-years of exposure.

Adverse reactions reported as reasons for discontinuation of treatment

In the pre-marketing pooled 8-week placebo-controlled studies in patients with MDD, 1,834 patients were exposed to desvenlafaxine (50 to 400 mg).Of the 1,834 patients, 12% discontinued treatment due to an adverse reaction, compared with 3% of the 1,116 placebo-treated patients. At the recommended dose of 50 mg, the discontinuation rate due to an adverse reaction for desvenlafaxine (4.1%) was similar to the rate for placebo (3.8%). For the 100 mg dose of desvenlafaxine the discontinuation rate due to an adverse reaction was 8.7%.

The most common adverse reactions leading to discontinuation in at least 2% and at a rate greater than placebo of the desvenlafaxine treated patients in the short-term studies, up to 8 weeks, were: nausea (4%); dizziness, headache and vomiting (2% each). In a longer-term study, up to 9 months, the most common was vomiting (2%).

Common adverse reactions in placebo-controlled MDD studies

The most commonly observed adverse reactions in desvenlafaxine treated MDD patients in pre-marketing pooled 8-week, placebo-controlled, fixed-dose studies (incidence ≥ 5% and at least twice the rate of placebo in the 50 or 100 mg dose groups) were: nausea, dizziness, insomnia, hyperhidrosis, constipation, somnolence, decreased appetite, anxiety, and specific male sexual function disorders.

Table 2 shows the incidence of common adverse reactions that occurred in ≥ 2% of desvenlafaxine treated MDD patients and twice the rate of placebo at any dose in the pooled 8-week, placebo-controlled, fixed dose clinical studies

Table 2: Common Adverse Reactions (≥ 2% in any Fixed-Dose Groupand Twice the Rate of Placebo) in Pre-marketing Pooled MDD 8-Week Placebo-Controlled Studies

 | Percentage of Patients Reporting Reaction
 |  | Desvenlafaxine
System Organ Class Preferred Term | Placebo (n=636) | 50 mg (n=317) | 100 mg (n=424) | 200 mg (n=307) | 400 mg (n=317)
Cardiac disorders
Blood pressure increased | 1 | 1 | 1 | 2 | 2
Gastrointestinal disorders
Nausea | 10 | 22 | 26 | 36 | 41
Dry mouth | 9 | 11 | 17 | 21 | 25
Constipation | 4 | 9 | 9 | 10 | 14
Vomiting | 3 | 3 | 4 | 6 | 9
General disorders and administration site conditions
Fatigue | 4 | 7 | 7 | 10 | 11
Chills | 1 | 1 | <1 | 3 | 4
Feeling jittery | 1 | 1 | 2 | 3 | 3
Metabolism and nutrition disorders
Decreased appetite | 2 | 5 | 8 | 10 | 10
Nervous system disorders
Dizziness | 5 | 13 | 10 | 15 | 16
Somnolence | 4 | 4 | 9 | 12 | 12
Tremor | 2 | 2 | 3 | 9 | 9
Disturbance in attention | <1 | <1 | 1 | 2 | 1
Psychiatric disorders
Insomnia | 6 | 9 | 12 | 14 | 15
Anxiety | 2 | 3 | 5 | 4 | 4
Nervousness | 1 | <1 | 1 | 2 | 2
Abnormal dreams | 1 | 2 | 3 | 2 | 4
Renal and urinary disorders
Urinary hesitation | 0 | <1 | 1 | 2 | 2
Respiratory, thoracic and mediastinal disorders
Yawning | <1 | 1 | 1 | 4 | 3
Skin and subcutaneous tissue disorders
Hyperhidrosis | 4 | 10 | 11 | 18 | 21
Special Senses
Vision blurred | 1 | 3 | 4 | 4 | 4
Mydriasis | <1 | 2 | 2 | 6 | 6
Vertigo | 1 | 2 | 1 | 5 | 3
Tinnitus | 1 | 2 | 1 | 1 | 2
Dysgeusia | 1 | 1 | 1 | 1 | 2
Vascular disorders
Hot flush | <1 | 1 | 1 | 2 | 2

Sexual function adverse reactions

Table 3 shows the incidence of sexual function adverse reactions that occurred in ≥ 2% of desvenlafaxine treated MDD patients in any fixed-dose group (pre-marketingpooled 8-week, placebo-controlled, fixed -dose, clinical studies).

Table 3: Sexual Function Adverse Reactions (≥2% in Menor Womenin any Desvenlafaxine Group) During the On-Therapy Period

 |  | Desvenlafaxine
 | Placebo (n=239) | 50 mg (n=108) | 100 mg (n=157) | 200 mg (n=131) | 400 mg (n=154)
Men only
Anorgasmia | 0 | 0 | 3 | 5 | 8
Libido decreased | 1 | 4 | 5 | 6 | 3
Orgasm abnormal | 0 | 0 | 1 | 2 | 3
Ejaculation delayed | <1 | 1 | 5 | 7 | 6
Erectile dysfunction | 1 | 3 | 6 | 8 | 11
Ejaculation disorder | 0 | 0 | 1 | 2 | 5
Ejaculation failure | 0 | 1 | 0 | 2 | 2
Sexual dysfunction | 0 | 1 | 0 | 0 | 2
 | Placebo (n=397) | Desvenlafaxine
 | Placebo (n=397) | 50 mg (n=209) | 100 mg (n=267) | 200 mg (n=176) | 400 mg (n=163)
Women only
Anorgasmia | 0 | 1 | 1 | 0 | 3

Other adverse reactions observed in premarketing and postmarketing clinical studies

Other infrequent adverse reactions, not described elsewhere in the label, occurring at an incidence of < 2% in MDD patients treated with desvenlafaxine were:

Cardiac disorders – tachycardia.

General disorders and administration site conditions – Asthenia.

Investigations – Weight increased, liver function test abnormal, blood prolactin increased.

Musculoskeletal and connective tissue disorders – Musculoskeletal stiffness.

Nervous system disorders –Syncope, convulsion, dystonia.

Psychiatric disorders – Depersonalization, bruxism.

Renal and urinary disorders – Urinary retention.

Skin and subcutaneous tissue disorders – Rash, alopecia, photosensitivity reaction, angioedema.

In clinical studies, there were uncommon reports of ischemic cardiac adverse reactions, including myocardial ischemia, myocardial infarction, and coronary occlusion requiring revascularization; these patients had multiple underlying cardiac risk factors. More patients experienced these events during desvenlafaxine treatment as compared to placebo.

Laboratory, ECG and vital sign changes observed in MDD clinical studies

The following changes were observed in pre-marketing placebo-controlled, short-term MDD studies with desvenlafaxine.

Lipids

Elevations in fasting serum total cholesterol, LDL (low density lipoproteins) cholesterol, and triglycerides occurred in the controlled studies. Some of these abnormalities were considered potentially clinically significant.

The percentage of patients who exceeded a predetermined threshold value is shown in Table 4.

Table 4: Incidence (%) of Patients With Lipid Abnormalities of Potential Clinical Significance*

 |  | Desvenlafaxine
 | Placebo | 50 mg | 100 mg | 200 mg | 400 mg
Total Cholesterol | 2 | 3 | 4 | 4 | 10
*(Increase of ≥ 50 mg/dl and an absolute value of ≥ 261 mg/dl)
LDL Cholesterol | 0 | 1 | 0 | 1 | 2
*(Increase ≥ 50 mg/dl and an absolute value of ≥ 190 mg/dl)
Triglycerides, fasting | 3 | 2 | 1 | 4 | 6
*(Fasting: ≥ 327 mg/dl)

Proteinuria

Proteinuria, greater than or equal to trace, was observed in the pre-marketingfixed-dose controlled studies (see Table 5). This proteinuria was not associated with increases in BUN or creatinine and was generally transient.

Table 5: Incidence (%) of Patients with Proteinuria in the Fixed-dose Clinical Studies

 |  | Desvenlafaxine
 | Placebo | 50 mg | 100 mg | 200 mg | 400 mg
Proteinuria | 4 | 6 | 8 | 5 | 7

Vital sign changes

Table 6 summarizes the changes that were observed in placebo-controlled, short-term, pre-marketing studies with desvenlafaxine in patients with MDD (doses 50 to 400 mg).

Table 6: Mean Changes in Vital Signs at Final on Therapy for All Short-term, Fixed-dose Controlled Studies

 |  | Desvenlafaxine
 | Placebo | 50 mg | 100 mg | 200 mg | 400 mg
Blood pressure
Supine systolic bp (mm Hg) | -1.4 | 1.2 | 2 | 2.5 | 2.1
Supine diastolic bp (mm Hg) | -0.6 | 0.7 | 0.8 | 1.8 | 2.3
Pulse rate
Supine pulse (bpm) | -0.3 | 1.3 | 1.3 | 0.9 | 4.1
Weight (kg) | 0 | -0.4 | -0.6 | -0.9 | -1.1

Treatment with desvenlafaxine at all doses from 50 mg per day to 400 mg per day in controlled studies was associated with sustained hypertension, defined as treatment-emergent supine diastolic blood pressure (SDBP) ≥90 mm Hg and ≥10 mm Hg above baseline for 3 consecutive on-therapy visits (see Table 7). Analyses of patients in desvenlafaxine pre-marketing short-term controlled studies who met criteria for sustained hypertension revealed a consistent increase in the proportion of patients who developed sustained hypertension. This was seen at all doses with a suggestion of a higher rate at 400 mg per day.

Table 7: Proportion of Patients with Sustained Elevation of Supine Diastolic Blood Pressure

Treatment Group | Proportion of Patients with Sustained Hypertension
Placebo | 0.5%
Desvenlafaxine 50 mg per day | 1.3%
Desvenlafaxine 100 mg per day | 0.7%
Desvenlafaxine 200 mg per day | 1.1%
Desvenlafaxine 400 mg per day | 2.3%

Orthostatic hypotension

In the pre-marketingshort-term, placebo-controlled clinical studies with doses of 50 to 400 mg, systolic orthostatic hypotension (decrease ≥30 mm Hg from supine to standing position) occurred more frequently in patients ≥65 years of age receiving desvenlafaxine (8%, 7/87) versus placebo (2.5%, 1/40), compared to patients <65 years of age receiving desvenlafaxine (0.9%, 18/1,937) versus placebo (0.7%, 8/1,218).

6.2 Postmarketing Experience

The following adverse reaction has been identified during post-approval use of desvenlafaxine. Because these reactions are reported voluntarily from a population of uncertain size, it is not always possible to reliably estimate their frequency or establish a causal relationship to drug exposure:

Skin and subcutaneous tissue disorders –Stevens-Johnson syndrome.
Gastrointestinal system – Acute pancreatitis.
Cardiovascular system – Takotsubo cardiomyopathy.

7 DRUG INTERACTIONS

7.1 Monoamine Oxidase Inhibitors (MAOI)

Do not use MAOIs intended to treat psychiatric disorders with desvenlafaxine or within 7 days of stopping treatment with desvenlafaxine. Do not use desvenlafaxine within 14 days of stopping an MAOI intended to treat psychiatric disorders. In addition, do not start desvenlafaxine in a patient who is being treated with linezolid or intravenous methylene blue[see Dosage and Administration (2.6), Contraindications (4) and Warnings and Precautions (5.2)].

7.2 Serotonergic Drugs

Based on the mechanism of action of desvenlafaxine and the potential for serotonin syndrome, caution is advised when desvenlafaxine is co-administered with other drugs that may affect the serotonergic neurotransmitter systems[see Dosage and Administration (2.6), Contraindications (4) and Warnings and Precautions (5.2)].

7.3 Drugs that Interfere with Hemostasis (e.g., NSAIDs, Aspirin, and Warfarin)

Serotonin release by platelets plays an important role in hemostasis. Epidemiological studies of case-control and cohort design that have demonstrated an association between use of psychotropic drugs that interfere with serotonin reuptake and the occurrence of upper gastrointestinal bleeding. These studies have also shown that concurrent use of an NSAID or aspirin may potentiate this risk of bleeding. Altered anticoagulant effects, including increased bleeding, have been reported when SSRIs and SNRIs are co-administered with warfarin. Patients receiving warfarin therapy should be carefully monitored when desvenlafaxine is initiated or discontinued [see Warnings and Precautions (5.4)].

7.4 Potential for Desvenlafaxine to Affect Other Drugs

Based on in vitro data, no dose adjustment is required for desvenlafaxine when used concomitantly with inhibitors of CYP3A4 and CYP1A1, 1A2, 2A6, 2D6, 2C8, 2C9, 2C19, 2E1, and the P-glycoprotein transporter. Clinical studies have demonstrated no clinically significant pharmacokinetic interaction between desvenlafaxine and strong CYP 3A4 inhibitors (Figure 1).

7.5 Potential for Desvenlafaxine to Affect Other Drugs

Clinical studies have shown that desvenlafaxine does not have a clinically relevant effect on CYP2D6 metabolism at the dose of 100 mg daily (Figure 2). Substrates primarily metabolized by CYP2D6 (e.g., desipramine , atomoxetine, dextromethorphan, metoprolol, nebivolol, perphenazine, tolterodine) should be dosed at the original level when co-administered with desvenlafaxine 100 mg or lower or when desvenlafaxine is discontinued. Reduce the dose of these substrates by up to one-half if co-administered with 400 mg of desvenlafaxine.

No additional dose adjustment is required for concomitant use of substrates of CYP3A4, 1A2, 2A6, 2C8, 2C9, and 2C19 isozymes, and P-glycoprotein transporter. Clinical studies have demonstrated no clinically significant pharmacokinetic interaction between desvenlafaxine and CYP3A4 substrates (Figure 2).

Clinical studies have shown that desvenlafaxine (100 mg daily) does not have a clinically relevant effect on tamoxifen and aripiprazole, compounds that are metabolized by a combination of both CYP2D6 and CYP3A4 enzymes (Figure 2).

In vitro studies showed minimal inhibitory effect of desvenlafaxine on the CYP2D6 isoenzyme.

In vitro, desvenlafaxine does not inhibit or induce the CYP3A4 isozyme.

In vitro, desvenlafaxine does not inhibit CYP1A2, 2A6, 2C8, 2C9, and 2C19, isozymes, and P-glycoprotein transporter and would not be expected to affect the pharmacokinetics of drugs that are substrates of these CYP isozymes and transporter.

7.6 Other Drugs Containing Desvenlafaxine or Venlafaxine

Avoid use of desvenlafaxine with other desvenlafaxine-containing products or venlafaxine products. The concomitant use of desvenlafaxine with other desvenlafaxine-containing products or venlafaxine will increase desvenlafaxine blood levels and increase dose-related adverse reactions [see Adverse Reactions (6)].

7.7 Ethanol

A clinical study has shown that desvenlafaxine does not increase the impairment of mental and motor skills caused by ethanol. However, as with all CNS-active drugs, patients should be advised to avoid alcohol consumption while taking desvenlafaxine.

7.8 Drug-Laboratory Test Interactions

False-positive urine immunoassay screening tests for phencyclidine (PCP) and amphetamine have been reported in patients taking desvenlafaxine. This is due to lack of specificity of the screening tests. False positive test results may be expected for several days following discontinuation of desvenlafaxine therapy. Confirmatory tests, such as gas chromatography/mass spectrometry, will distinguish desvenlafaxine from PCP and amphetamine.

8 USE IN SPECIFIC POPULATIONS

8.1 Pregnancy

Pregnancy Category C

Risk summary

There are no adequate and well-controlled studies of desvenlafaxine in pregnant women. In reproductive developmental studies in rats and rabbits with desvenlafaxine succinate, evidence of teratogenicity was not observed at doses up to 30 times a human dose of 100 mg per day (on a mg/m^2 basis) in rats, and up to 15 times a human dose of 100 mg per day (on a mg/m^2 basis) in rabbits. An increase in rat pup deaths was seen during the first 4 days of lactation when dosing occurred during gestation and lactation, at doses greater than 10 times a human dose of 100 mg per day (on a mg/m^2 basis). Desvenlafaxine should be used during pregnancy only if the potential benefits justify the potential risks to the fetus.

Clinical considerations

A prospective longitudinal study of 201 women with history of major depression who were euthymic at the beginning of pregnancy, showed women who discontinued antidepressant medication during pregnancy were more likely to experience a relapse of major depression than women who continued antidepressant medication.

Human data

Neonates exposed to SNRIs (Serotonin and Norepinephrine Reuptake Inhibitors), or SSRIs (Selective Serotonin Reuptake Inhibitors), late in the third trimester have developed complications requiring prolonged hospitalization, respiratory support, and tube feeding. Such complications can arise immediately upon delivery. Reported clinical findings have included respiratory distress, cyanosis, apnea, seizures, temperature instability, feeding difficulty, vomiting, hypoglycemia, hypotonia, hypertonia, hyperreflexia, tremor, jitteriness, irritability, and constant crying. These features are consistent with either a direct toxic effect of SSRIs and SNRIs or, possibly, a drug discontinuation syndrome. It should be noted that, in some cases, the clinical picture is consistent with serotonin syndrome [see Warnings and Precautions (5.2)].

Animal data

When desvenlafaxine succinate was administered orally to pregnant rats and rabbits during the period of organogenesis at doses up to 300 mg/kg/day and 75 mg/kg/day, respectively, no teratogenic effects were observed. These doses are 30 times a human dose of 100 mg per day (on a mg/m^2 basis) in rats and 15 times a human dose of 100 mg per day (on a mg/m^2 basis) in rabbits. However, fetal weights were decreased and skeletal ossification was delayed in rats in association with maternal toxicity at the highest dose, with a no-effect dose 10 times a human dose of 100 mg per day (on a mg/m^2 basis).

When desvenlafaxine succinate was administered orally to pregnant rats throughout gestation and lactation, there was a decrease in pup weights and an increase in pup deaths during the first four days of lactation at the highest dose of 300 mg/kg/day. The cause of these deaths is not known. The no-effect dose for rat pup mortality was 10 times a human dose of 100 mg per day (on a mg/m^2 basis). Post-weaning growth and reproductive performance of the progeny were not affected by maternal treatment with desvenlafaxine succinate at a dose 30 times a human dose of 100 mg per day (on a mg/m^2 basis).

8.3 Nursing Mothers

Desvenlafaxine (O-desmethylvenlafaxine) is excreted in human milk. Because of the potential for serious adverse reactions in nursing infants from desvenlafaxine, a decision should be made whether or not to discontinue nursing or to discontinue the drug, taking into account the importance of the drug to the mother.

8.4 Pediatric Use

Safety and effectiveness in pediatric patients have not been established [see Boxed Warning and Warnings and Precautions (5.1)]. Anyone considering the use of desvenlafaxine in a child or adolescent must balance the potential risks with the clinical need.

8.5 Geriatric Use

Of the 4,158 patients in clinical studies with desvenlafaxine, 6% were 65 years of age or older. No overall differences in safety or efficacy were observed between these patients and younger patients; however, in the short-term placebo-controlled studies, there was a higher incidence of systolic orthostatic hypotension in patients ≥65 years of age compared to patients <65 years of age treated with desvenlafaxine [see Adverse Reactions (6)]. For elderly patients, possible reduced renal clearance of desvenlafaxine should be considered when determining dose [see Dosage and Administration (2.2) and Clinical Pharmacology (12.3)].

SSRIs and SNRIs, including desvenlafaxine, have been associated with cases of clinically significant hyponatremia in elderly patients, who may be at greater risk for this adverse event [see Warnings and Precautions (5.9)].

8.6 Other Patient Factors

The effect of intrinsic patient factors on the pharmacokinetics of desvenlafaxine is presented in Figure 3.

Renal Impairment

In subjects with renal impairment the clearance of desvenlafaxine was decreased. In subjects with severe renal impairment (24-hr CrCl <30 mL/min, Cockcroft-Gault) and end-stage renal disease, elimination half-lives were significantly prolonged, increasing exposures to desvenlafaxine; therefore, dosage adjustment is recommended in these patients [see Dosage and Administration (2.2) and Clinical Pharmacology (12.3)].

Hepatic Impairment

The mean terminal half life (t1/2) changed from approximately 10 hours in healthy subjects and subjects with mild hepatic impairment to 13 and 14 hours in moderate and severe hepatic impairment, respectively. The recommended dose in patients with moderate to severe hepatic impairment is 50 mg per day. Dose escalation above 100 mg per day is not recommended [see Clinical Pharmacology (12.3)].

9 DRUG ABUSE AND DEPENDENCE

9.1 Controlled Substance

Desvenlafaxine is not a controlled substance.

10 OVERDOSAGE

10.1 Human Experience with Overdosage

There is limited clinical trial experience with desvenlafaxine succinate overdosage in humans. However, desvenlafaxine is the major active metabolite of venlafaxine. Overdose experience reported with venlafaxine (the parent drug of desvenlafaxine) is presented below; the identical information can be found in the Overdosagesection of the venlafaxine package insert.

In postmarketing experience, overdose with venlafaxine (the parent drug of desvenlafaxine) has occurred predominantly in combination with alcohol and/or other drugs. The most commonly reported events in overdosage include tachycardia, changes in level of consciousness (ranging from somnolence to coma), mydriasis, seizures, and vomiting. Electrocardiogram changes (e.g., prolongation of QT interval, bundle branch block, QRS prolongation), sinus and ventricular tachycardia, bradycardia, hypotension, rhabdomyolysis, vertigo, liver necrosis, serotonin syndrome, and death have been reported.

Published retrospective studies report that venlafaxine overdosage may be associated with an increased risk of fatal outcomes compared to that observed with SSRI antidepressant products, but lower than that for tricyclic antidepressants. Epidemiological studies have shown that venlafaxine-treated patients have a higher pre-existing burden of suicide risk factors than SSRI-treated patients. The extent to which the finding of an increased risk of fatal outcomes can be attributed to the toxicity of venlafaxine in overdosage, as opposed to some characteristic(s) of venlafaxine-treated patients, is not clear.

10.2 Management of Overdosage

No specific antidotes for desvenlafaxine are known. In managing over dosage, consider the possibility of multiple drug involvement. In case of overdose, call Poison Control Center at 1-800-222-1222 for latest recommendations.

11 DESCRIPTION

Desvenlafaxine extended-release tablets for oral administration contains desvenlafaxine, a structurally novel SNRI for the treatment of MDD. Desvenlafaxine (O-desmethylvenlafaxine) is the major active metabolite of the antidepressant venlafaxine, a medication used to treat major depressive disorder.

Desvenlafaxine is designated RS-4-[2-dimethylamino-1-(1-hydroxycyclohexyl)ethyl]phenol and has the empirical formula of C16H25NO2. Desvenlafaxine has a molecular weight of 263.38. The structural formula is shown below.

* Chiral Centre

Desvenlafaxine is a white to off-white crystalline powder that is sparingly soluble in dimethyl sulfoxide. The solubility of desvenlafaxine is pH dependent.

Desvenlafaxine is formulated as an extended-release tablet for once-a-day oral administration.

Each 50 mg or 100 mg extended-release tablet contains 50 or 100 mg of desvenlafaxine, respectively.

Inactive ingredients for the 50 mg tablet consist of alginic acid, citric acid monohydrate powder, hypromellose, microcrystalline cellulose, povidone, talc, magnesium stearate and film coating, which consist of hypromellose, titanium dioxide, polyethylene glycol, talc, and iron oxide red.

Inactive ingredients for the 100 mg tablet consist of alginic acid, citric acid monohydrate powder, hypromellose, microcrystalline cellulose, povidone, talc, magnesium stearate and film coating, which consist of hypromellose, titanium dioxide, polyethylene glycol, iron oxide red, and iron oxide black.

12 CLINICAL PHARMACOLOGY

12.1 Mechanism of Action

The exact mechanism of the antidepressant action of desvenlafaxine is unknown, but is thought to be related to the potentiation of serotonin and norepinephrine in the central nervous system, through inhibition of their reuptake. Non-clinical studies have shown that desvenlafaxine is a potent and selective serotonin and norepinephrine reuptake inhibitor (SNRI).

12.2 Pharmacodynamics

Desvenlafaxine lacked significant affinity for numerous receptors, including muscarinic-cholinergic, H1-histaminergic, or α1-adrenergic receptors in vitro. Desvenlafaxine also lacked monoamine oxidase (MAO) inhibitory activity.

ECG changes

Electrocardiograms were obtained from 1,492 desvenlafaxine treated patients with major depressive disorder and 984 placebo-treated patients in clinical studies lasting up to 8 weeks. No clinically relevant differences were observed between desvenlafaxine treated and placebo-treated patients for QT, QTc, PR, and QRS intervals. In a thorough QTc study with prospectively determined criteria, desvenlafaxine did not cause QT prolongation. No difference was observed between placebo and desvenlafaxine treatments for the QRS interval.

12.3 Pharmacokinetics

The single-dose pharmacokinetics of desvenlafaxine are linear and dose-proportional in a dose range of 50 to 600 mg per day. With once-daily dosing, steady-state plasma concentrations are achieved within approximately 4 to 5 days. At steady-state, multiple-dose accumulation of desvenlafaxine is linear and predictable from the single-dose pharmacokinetic profile.

Absorption and distribution

The absolute oral bioavailability of desvenlafaxine after oral administration is about 80%.

A food-effect study involving administration of desvenlafaxine extended-release tablets to healthy subjects under fasting and fed conditions (high-fat meal, 800 to 1000 calories) indicated that desvenlafaxine Cmax was increased about 16% in the fed state, while the AUCs were similar. This difference is not expected to be clinically significant; therefore, desvenlafaxine extended-release tablets can be taken without regard to meals [see Dosage and Administration (2.1)].

The plasma protein binding of desvenlafaxine is low (30%) and is independent of drug concentration. The desvenlafaxine volume of distribution at steady-state following intravenous administration is 3.4 L/kg, indicating distribution into nonvascular compartments.

Metabolism and elimination

Desvenlafaxine is primarily metabolized by conjugation (mediated by UGT isoforms) and, to a minor extent, through oxidative metabolism. CYP3A4 is the cytochrome P450 isozyme mediating the oxidative metabolism (N-demethylation) of desvenlafaxine. The CYP2D6 metabolic pathway is not involved, and after administration of 100 mg, the pharmacokinetics of desvenlafaxine was similar in subjects with CYP2D6 poor and extensive metabolizer phenotype. Approximately 45% of desvenlafaxine is excreted unchanged in urine at 72 hours after oral administration. Approximately 19% of the administered dose is excreted as the glucuronide metabolite and <5% as the oxidative metabolite (N, O-didesmethylvenlafaxine) in urine.

Drug interaction studies

Inhibitors of CYP3A4 (ketoconazole)

CYP3A4 is a minor pathway for the metabolism of desvenlafaxine. In a clinical study, ketoconazole (200 mg BID) increased the area under the concentration vs. time curve (AUC) of desvenlafaxine (400 mg single dose) by about 43% and Cmax by about 8%. Concomitant use of desvenlafaxine with potent inhibitors of CYP3A4 may result in higher concentrations of desvenlafaxine.

Inhibitors of other CYP enzymes

Based on in vitro data, drugs that inhibit CYP isozymes 1A1, 1A2, 2A6, 2D6, 2C8, 2C9, 2C19, and 2E1 are not expected to have significant impact on the pharmacokinetic profile of desvenlafaxine.

Drugs metabolized by CYP2D6 (e.g. desipramine, dextromethorphan, metoprolol, atomoxetine)

In vitro studies showed minimal inhibitory effect of desvenlafaxine on CYP2D6. Clinical studies have shown that desvenlafaxine does not have a clinically relevant effect on CYP2D6 metabolism at the dose of 100 mg daily. When desvenlafaxine succinate was administered at a dose of 100 mg daily in conjunction with a single 50 mg dose of desipramine, a CYP2D6 substrate, the Cmax and AUC of desipramine increased approximately 25% and 17%, respectively. When 400 mg (8 times the recommended 50 mg dose) was administered, the Cmax and AUC of desipramine increased approximately 50% and 90%, respectively. Concomitant use of desvenlafaxine with a drug metabolized by CYP2D6 can result in higher concentrations of that drug [see Drug Interactions (7.5)].

Drugs metabolized by CYP3A4 (midazolam)

In vitro, desvenlafaxine does not inhibit or induce the CYP3A4 isozyme. In a clinical study, desvenlafaxine 400 mg daily (8 times the recommended 50 mg dose) was co-administered with a single 4 mg dose of midazolam (a CYP3A4 substrate). The AUC and Cmax of midazolam decreased by approximately 31% and 16%, respectively. Concomitant use of desvenlafaxine with a drug metabolized by CYP3A4 can result in lower exposures to that drug.

Drugs metabolized by CYP1A2, 2A6, 2C8, 2C9 and 2C19

In vitro, desvenlafaxine does not inhibit CYP1A2, 2A6, 2C8, 2C9, and 2C19 isozymes and would not be expected to affect the pharmacokinetics of drugs that are metabolized by these CYP isozymes.

In vitro, desvenlafaxine is not a substrate or an inhibitor for the P-glycoprotein transporter. The pharmacokinetics of desvenlafaxine are unlikely to be affected by drugs that inhibit the P-glycoprotein transporter, and desvenlafaxine is not likely to affect the pharmacokinetics of drugs that are substrates of the P-glycoprotein transporter.

Special populations

Age

In a study of healthy subjects administered doses of up to 300 mg, there was an approximate 32% increase in Cmax and a 55% increase in AUC in subjects older than 75 years of age (n = 17), compared with subjects 18 to 45 years of age (n = 16). Subjects 65 to 75 years of age (n = 15) had no change in Cmax, but an approximately 32% increase in AUC, compared to subjects 18 to 45 years of age [see Dosage and Administration (2.2)].

Gender

In a study of healthy subjects administered doses of up to 300 mg, women had an approximately 25% higher Cmax and an approximately 10% higher AUC than age-matched men. No adjustment of dosage on the basis of gender is needed.

Race

Pharmacokinetic analysis showed that race (White, n = 466; Black, n = 97; Hispanic, n = 39; Other, n = 33) had no apparent effect on the pharmacokinetics of desvenlafaxine. No adjustment of dosage on the basis of race is needed.

Hepatic insufficiency

The disposition of desvenlafaxine succinate after administration of 100 mg was studied in subjects with mild (Child-Pugh A, n = 8), moderate (Child-Pugh B, n = 8), and severe (Child-Pugh C, n = 8) hepatic impairment and to healthy subjects (n = 12).

Average AUC was increased by approximately 31% and 35% in patients with moderate and severe hepatic impairment, respectively, as compared to healthy subjects. Average AUC values were similar in subjects with mild hepatic impairment and healthy subjects (< 5% difference).

Systemic clearance (CL/F) was decreased by approximately 20% and 36% in patients with moderate and severe hepatic impairment, respectively, as compared to healthy subjects. CL/F values were comparable in mild hepatic impairment and healthy subjects (< 5% difference).

The mean t1/2 changed from approximately 10 hours in healthy subjects and subjects with mild hepatic impairment to 13 and 14 hours in moderate and severe hepatic impairment, respectively. The recommended dose in patients with hepatic impairment is 50 mg per day. Dose escalation above 100 mg per day is not recommended [see Use in Specific Populations (8.6)].

Renal insufficiency

The disposition of desvenlafaxine after administration of 100 mg was studied in subjects with mild (n = 9), moderate (n = 8), severe (n = 7) and end-stage renal disease (ESRD) (n = 9) requiring dialysis and in healthy, age-matched control subjects (n = 8). Elimination was significantly correlated with creatinine clearance. Increases in AUCs of about 42% in mild renal impairment (24-hr CrCl = 50 to 80 mL/min, Cockcroft-Gault [C-G]), about 56% in moderate renal impairment (24-hr CrCl = 30 to 50 mL/min, C-G), about 108% in severe renal impairment (24-hr CrCl ≤30 mL/min, C-G), and about 116% in ESRD subjects were observed, compared with healthy, age-matched control subjects.

The mean terminal half-life (t1/2) was prolonged from 11.1 hours in the control subjects to approximately 13.5, 15.5, 17.6, and 22.8 hours in mild, moderate, severe renal impairment and ESRD subjects, respectively. Less than 5% of the drug in the body was cleared during a standard 4-hour hemodialysis procedure.

The maximum recommended dose in patients with moderate renal impairment is 50 mg per day. Dosage adjustment of 50 mg every other day is recommended in patients with severe renal impairment or ESRD [see Dosage and Administration (2.2) and Use in Specific Populations (8.6)].

13 NONCLINICAL TOXICOLOGY

13.1 Carcinogenesis, Mutagenesis, Impairment of Fertility

Carcinogenesis

Desvenlafaxine succinate administered by oral gavage to mice and rats for 2 years did not increase the incidence of tumors in either study.

Mice received desvenlafaxine succinate at dosages up to 500/300 mg/kg/day (dosage lowered after 45 weeks of dosing). The 300 mg/kg/day dose is 15 times a human dose of 100 mg per day on a mg/m^2 basis.

Rats received desvenlafaxine succinate at dosages up to 300 mg/kg/day (males) or 500 mg/kg/day (females). The highest dose is 29 (males) or 48 (females) times a human dose of 100 mg per day on a mg/m^2 basis.

Mutagenesis

Desvenlafaxine was not mutagenic in the in vitro bacterial mutation assay (Ames test) and was not clastogenic in an in vitro chromosome aberration assay in cultured CHO cells, an in vivo mouse micronucleus assay, or an in vivo chromosome aberration assay in rats. Additionally, desvenlafaxine was not genotoxic in the in vitro CHO mammalian cell forward mutation assay and was negative in the in vitro BALB/c-3T3 mouse embryo cell transformation assay.

Impairment of fertility

When desvenlafaxine succinate was administered orally to male and female rats, fertility was reduced at the high dose of 300 mg/kg/day, which is 30 times a human dose of 100 mg per day (on a mg/m^2 basis). There was no effect on fertility at 100 mg/kg/day, approximately 10 times a human dose of 100 mg per day (on a mg/m^2 basis).

14 CLINICAL STUDIES

The efficacy of desvenlafaxine as a treatment for depression was established in four 8-week, randomized, double-blind, placebo-controlled, fixed-dose studies (at doses of 50 mg per day to 400 mg per day) in adult outpatients who met the Diagnostic and Statistical Manual of Mental Disorders (DSM-IV) criteria for major depressive disorder. In the first study, patients received 100 mg (n = 114), 200 mg (n = 116), or 400 mg (n = 113) of desvenlafaxine once daily, or placebo (n = 118). In a second study, patients received either 200 mg (n = 121) or 400 mg (n = 124) of desvenlafaxine once daily, or placebo (n = 124). In two additional studies, patients received 50 mg (n = 150 and n = 164) or 100 mg (n = 147 and n = 158) of desvenlafaxine once daily, or placebo (n = 150 and n = 161).

Desvenlafaxine showed superiority over placebo as measured by improvement in the 17-item Hamilton Rating Scale for Depression (HAM-D17) total score in four studies and overall improvement, as measured by the Clinical Global Impressions Scale - Improvement (CGI-I), in three of the four studies. In studies directly comparing 50 mg per day and 100 mg per day there was no suggestion of a greater effect with the higher dose and adverse reactions and discontinuations were more frequent at higher doses [see Dosage and Administration (2.1)].

Table 8: Primary Efficacy (HAM-D17) Results for Short-term Studies

 |  |  | Desvenlafaxine
Study No. | Primary Endpoint: HAM-D17 | Placebo | 50 mg/day | 100 mg/day | 200 mg/day | 400 mg/day
1 | Baseline Score (SDa) | 23.1 (2.5) |  | 23.2 (2.5) | 22.9 (2.4) | 23 (2.2)
1 | Difference from Placebo (95% CI c) |  |  | -2.9b (-5.1, -0.8) | -2 | -3.1b (-5.2, -0.9)
2 | Baseline Score (SDa) | 25.3 (3.3) |  |  | 24.8 (2.9) | 25.2 (3.2)
2 | Difference from Placebo (95% CI c) |  |  |  | -3.3b (-5.3, -1.2) | -2.8b (-4.8, -0.7)
3 | Baseline Score (SDa) | 23 (2.6) | 23.4 (2.6) | 23.4 (2.6)
3 | Difference from Placebo (95% CI c) |  | -1.9b (-3.5, -0.3) | -1.5
4 | Baseline Score (SDa) | 24.3 (2.6) | 24.3 (2.4) | 24.4 (2.7)
4 | Difference from Placebo (95% CI c) |  | -2.5b (-4.1, -0.9) | -3b (-4.7, -1.4)
a Standard deviation;
b Adjusted p-value < 0.05;
c Difference between least squares means at final evaluation, calculated as drug response minus placebo response; unadjusted 95% confidence intervals

Analyses of the relationships between treatment outcome and age and treatment outcome and gender did not suggest any differential responsiveness on the basis of these patient characteristics. There was insufficient information to determine the effect of race on outcome in these studies.

16 HOW SUPPLIED/STORAGE AND HANDLING

Desvenlafaxine extended-release tablets are available as follows:

50 mg, light pink colored, diamond shaped, biconvex tablets, debossed with ‘L189’ on one side and plain on other side.

NDC 46708-152-30, bottle of 30 tablets

NDC 46708-152-90, bottle of 90 tablets

100 mg, dark brown to red colored, diamond shaped, biconvex tablets, debossed with ‘L190’ on one side and plain on other side.

NDC 46708-153-30, bottle of 30 tablets

NDC 46708-153-90, bottle of 90 tablets

Store at 20° to 25°C (68° to 77°F); excursions permitted to 15° to 30°C (59° to 86°F) [see USP Controlled Room Temperature].

Each 50 mg or 100 mg extended-release tablet contains 50 or 100 mg of desvenlafaxine, respectively.

17 PATIENT COUNSELING INFORMATION

See FDA-approved patient labeling (Medication Guide).

Advise patients, their families, and their caregivers about the benefits and risks associated with treatment with desvenlafaxine and counsel them in its appropriate use.

Advise patients, their families, and their caregivers to read the Medication Guide and assist them in understanding its contents. The complete text of the Medication Guide is reprinted at the end of this document.

Suicide Risk
Advise patients, their families and caregivers to look for the emergence of suicidality, especially early during treatment and when the dose is adjusted up or down [see Boxed Warning and Warnings and Precautions (5.1)].

Concomitant Medication
Advise patients taking desvenlafaxine extended-release tablets not to use concomitantly other products containing desvenlafaxine or venlafaxine. Healthcare professionals should instruct patients not to take desvenlafaxine with an MAOI or within 14 days of stopping an MAOI and to allow 7 days after stopping desvenlafaxine before starting an MAOI [see Contraindications (4)].

Serotonin Syndrome
Caution patients about the risk of serotonin syndrome, particularly with the concomitant use of desvenlafaxine with other serotonergic agents (including triptans, tricyclic antidepressants, fentanyl, lithium, tramadol, tryptophan, buspirone, amphetamines, and St. John's Wort supplements) [see Warnings and Precautions (5.2)].

Elevated Blood Pressure
Advise patients that they should have regular monitoring of blood pressure when taking desvenlafaxine [see Warnings and Precautions (5.3)].

Abnormal Bleeding
Patients should be cautioned about the concomitant use of desvenlafaxine and NSAIDs, aspirin, warfarin, or other drugs that affect coagulation since combined use of psychotropic drugs that interfere with serotonin reuptake and these agents has been associated with an increased risk of bleeding [see Warnings and Precautions (5.4)].

Angle Closure Glaucoma
Patients should be advised that taking desvenlafaxine can cause mild pupillary dilation, which in susceptible individuals, can lead to an episode of angle closure glaucoma. Pre-existing glaucoma is almost always open-angle glaucoma because angle closure glaucoma, when diagnosed, can be treated definitively with iridectomy. Open-angle glaucoma is not a risk factor for angle closure glaucoma. Patients may wish to be examined to determine whether they are susceptible to angle closure, and have a prophylactic procedure (e.g., iridectomy), if they are susceptible [see Warnings and Precautions (5.5)].

Activation of Mania/Hypomania
Advise patients, their families and caregivers to observe for signs of activation of mania/hypomania [see Warnings and Precautions (5.6)].

Discontinuation
Advise patients not to stop taking desvenlafaxine without talking first with their healthcare professional. Patients should be aware that discontinuation effects may occur when stopping desvenlafaxine [see Warnings and Precautions (5.7) and Adverse Reactions (6.1)].

Switching Patients From Other Antidepressants to Desvenlafaxine
Discontinuation symptoms have been reported when switching patients from other antidepressants, including venlafaxine, to desvenlafaxine. Tapering of the initial antidepressant may be necessary to minimize discontinuation symptoms.

Interference with Cognitive and Motor Performance
Caution patients about operating hazardous machinery, including automobiles, until they are reasonably certain that desvenlafaxine therapy does not adversely affect their ability to engage in such activities.

Alcohol
Advise patients to avoid alcohol while taking desvenlafaxine [see Drug Interactions (7.7)].

Allergic Reactions
Advise patients to notify their physician if they develop allergic phenomena such as rash, hives, swelling, or difficulty breathing.

Pregnancy
Advise patients to notify their physician if they become pregnant or intend to become pregnant during therapy [see Use in Specific Populations (8.1)].

Nursing
Advise patients to notify their physician if they are breastfeeding an infant [see Use in Specific Populations (8.3)].

Residual Inert Matrix Tablet
Patients receiving desvenlafaxine may notice an inert matrix tablet passing in the stool or via colostomy. Patients should be informed that the active medication has already been absorbed by the time the patient sees the inert matrix tablet.

Medication Guide

DESVENLAFAXINE extended-release tablets
(des VEN la FAX een)
Read this Medication Guide before you start taking desvenlafaxine and each time you get a refill. There may be new information. This information does not take the place of talking to your healthcare provider about your medical condition or treatment.
Antidepressant Medicines, Depression and Other Serious Mental Illnesses, and Suicidal Thoughts or Actions
Talk to your healthcare provider about:
• all risks and benefits of treatment with antidepressant medicines
• all treatment choices for depression or other serious mental illness
What is the most important information I should know about antidepressant medicines, depression and other serious mental illnesses, and suicidal thoughts or actions?
1. Antidepressant medicines may increase suicidal thoughts or actions in some children, teenagers, and young adults within the first few months of treatment.
2. Depression and other serious mental illnesses are the most important causes of suicidal thoughts and actions. Some people may have a particularly high risk of having suicidal thoughts or actions. These include people who have (or have a family history of) bipolar illness (also called manic-depressive illness) or suicidal thoughts or actions.
3. How can I watch for and try to prevent suicidal thoughts and actions?
• Pay close attention to any changes, especially sudden changes, in mood, behaviors, thoughts, or feelings. This is very important when an antidepressant medicine is started or when the dose is changed.
• Call the healthcare provider right away to report new or sudden changes in mood, behavior, thoughts, or feelings.
• Keep all follow-up visits with the healthcare provider as scheduled. Call the healthcare provider between visits as needed, especially if you have concerns about symptoms.
Call a healthcare provider right away if you have any of the following symptoms, especially if they are new, worse, or worry you:

• thoughts about suicide or dying

• trouble sleeping (insomnia)

• attempts to commit suicide

• new or worse irritability

• new or worse depression

• acting aggressive, being angry, or violent

• new or worse anxiety

• acting on dangerous impulses

• feeling very agitated or restless

• an extreme increase in activity and talking (mania)

• panic attacks

• other unusual changes in behavior or mood

What else do I need to know about antidepressant medicines?
• Never stop an antidepressant medicine without first talking to a healthcare provider. Stopping an antidepressant medicine suddenly can cause other symptoms.
• Antidepressants are medicines used to treat depression and other illnesses. It is important to discuss all the risks of treating depression and also the risks of not treating it. Patients should discuss all treatment choices with the healthcare provider, not just the use of antidepressants.
• Antidepressant medicines have other side effects. Talk to the healthcare provider about the side effects of this medicine.
• Antidepressant medicines can interact with other medicines. Know all of the medicines that you take. Keep a list of all medicines to show the healthcare provider. Do not start new medicines without first checking with your healthcare provider.
• Not all antidepressant medicines prescribed for children are FDA approved for use in children. Talk to your child’s healthcare provider for more information.
Important Information about desvenlafaxine extended-release tablets
Read the patient information that comes with desvenlafaxine before you take desvenlafaxine and each time you refill your prescription. There may be new information. If you have questions, ask your healthcare provider. This information does not take the place of talking with your healthcare provider about your medical condition or treatment.
What is desvenlafaxine?
• Desvenlafaxine is a prescription medicine used to treat depression. Desvenlafaxine belongs to a class of medicines known as SNRIs (or serotonin-norepinephrine reuptake inhibitors).
Who should not take desvenlafaxine?
Do not takedesvenlafaxine if you:
• are allergic to desvenlafaxine, venlafaxine or any of the ingredients in desvenlafaxine extended-release tablets. See the end of this Medication Guide for a complete list of ingredients in desvenlafaxine extended-release tablets.
• take a monoamine oxidase inhibitor (MAOI). Ask your healthcare provider or pharmacist if you are not sure if you take an MAOI, including the antibiotic linezolid and the intravenous medicine methylene blue.
• have taken an MAOI within 7 days of stopping desvenlafaxine unless directed by your healthcare provider.
• have started desvenlafaxine and if you stopped taking an MAOI in the last 14 days unless directed by your healthcare provider.
What should I tell my healthcare provider before taking desvenlafaxine?
Tell your healthcare provider about all your medical conditions, including if you:
• have high blood pressure
• have heart problems
• have high cholesterol or high triglycerides
• have a history of a stroke
• have or had depression, suicidal thoughts or behavior
• have kidney problems
• have liver problems
• have or had bleeding problems
• have or had seizures or convulsions
• have mania or bipolar disorder
• have low sodium levels in your blood
• are pregnant or plan to become pregnant. It is not known if desvenlafaxine will harm your unborn baby.
• are breastfeeding. Desvenlafaxine can pass into your breast milk and may harm your baby. Talk with your healthcare provider about the best way to feed your baby if you take desvenlafaxine.
Serotonin syndrome
Rare, but potentially life-threatening conditions called serotonin syndrome can happen when medicines such as desvenlafaxine are taken with certain other medicines. Serotonin syndrome can cause serious changes in how your brain, muscles, heart and blood vessels, and digestive system work. Especially tell your healthcare provider if you take the following:
• amphetamines
• medicines to treat migraine headaches known as triptans
• medicines used to treat mood, anxiety, psychotic, or thought disorders, including tricyclics, lithium, selective serotonin reuptake inhibitors (SSRIs), serotonin norepinephrine reuptake inhibitors (SNRIs), or other dopamine antagonists, such as metoclopramide
• silbutramine
• tramadol
• St. John’s Wort
• MAOIs (including linezolid, an antibiotic and intravenous methylene blue)
• tryptophan supplements
Ask your healthcare provider if you are not sure if you are taking any of these medicines.
Before you take desvenlafaxine with any of these medicines, talk to your healthcare provider about serotonin syndrome. See “What are the possible side effects of desvenlafaxine?”
Do not take desvenlafaxine extended-release tablets with other medicines containing venlafaxine or desvenlafaxine.
How should I take desvenlafaxine?
• Take desvenlafaxine exactly as your healthcare provider has told you.
• Take desvenlafaxine at about the same time each day.
• Desvenlafaxine may be taken either with or without food.
• Swallow desvenlafaxine tablets whole, with fluid. Do not crush, cut, chew, or dissolve desvenlafaxine tablets because the tablets are time-released.
• When you take desvenlafaxine, you may see something in your stool that looks like a tablet. This is the empty shell from the tablet after the medicine has been absorbed by your body.
• It is common for antidepressant medicines such as desvenlafaxine to take several weeks before you start to feel better. Do not stop taking desvenlafaxine if you do not feel results right away.
• Do not stop taking or change the dose of desvenlafaxine without talking with your healthcare provider, even if you feel better.
• Talk with your healthcare provider about how long you should use desvenlafaxine. Take desvenlafaxine for as long as your healthcare provider tells you to.
• If you miss a dose of desvenlafaxine, take it as soon as you remember. If it is almost time for your next dose, skip the missed dose. Do not try to “make up” for the missed dose by taking two doses at the same time.
• Do not take more desvenlafaxine than prescribed by your healthcare provider. If you take more desvenlafaxine than the amount prescribed, contact your healthcare provider right away.
• If you take too much desvenlafaxine, call the Poison Control Center at 1-800-222-1222 or go to the nearest hospital emergency room right away.
Switching from other antidepressants
Side effects from discontinuing antidepressant medication have occurred when patients switched from other antidepressants, including venlafaxine, to desvenlafaxine. Your doctor may gradually reduce the dose of your initial antidepressant medication to help to reduce these side effects.
What should I avoid while taking desvenlafaxine?
• Do not drive a car or operate machinery until you know how desvenlafaxine affects you.
• Avoid drinking alcohol while taking desvenlafaxine.
What are the possible side effects of desvenlafaxine?
Desvenlafaxine can cause serious side effects, including:
• See the beginning of this Medication Guide - Antidepressant Medicines, Depression and other Serious Mental Illnesses, and Suicidal Thoughts or Actions.
• Serotonin syndrome. See “What should I tell my healthcare provider before taking desvenlafaxine?”
Get medical help right away if you think that you have these syndromes. Signs and symptoms of these syndromes may include one or more of the following:

• restlessness

• increase in blood pressure

• hallucinations (seeing and hearing things that are not real)

• diarrhea

• loss of coordination

• coma

• fast heart beat

• nausea

• increased body temperature

• vomiting

• muscle stiffness

• confusion

Desvenlafaxine may also cause other serious side effects, including:
• New or worsened high blood pressure (hypertension). Your healthcare provider should monitor your blood pressure before and while you are taking desvenlafaxine. If you have high blood pressure, it should be controlled before you start taking desvenlafaxine.
• Abnormal bleeding or bruising. Desvenlafaxine and other SNRIs/SSRIs may cause you to have an increased chance of bleeding. Taking aspirin, NSAIDs (non-steroidal anti-inflammatory drugs), or blood thinners may add to this risk. Tell your healthcare provider right away about any unusual bleeding or bruising.
Visual problems
•

eye pain

- changes in vision
- swelling or redness in or around the eye
- Only some people are at risk for these problems. You may want to undergo an eye examination to see if you are at risk and receive preventative treatment if you are.

Symptoms when stopping desvenlafaxine (discontinuation symptoms). Side effects may occur when stopping desvenlafaxine (discontinuation symptoms), especially when therapy is stopped suddenly. Your healthcare provider may want to decrease your dose slowly to help avoid side effects. Some of these side effects may include:

• dizziness

• anxiety

• nausea

• abnormal dreams

• headache

• tiredness

• irritability

• sweating

• sleeping problems (insomnia)

• diarrhea

• Seizures (convulsions)
• Low sodium levels in your blood. Symptoms of this may include: headache, difficulty concentrating, memory changes, confusion, weakness and unsteadiness on your feet. In severe or more sudden cases, symptoms can include: hallucinations (seeing or hearing things that are not real), fainting, seizures and coma. If not treated, severe low sodium levels could be fatal.
• Lung problems. Some people who have taken the medicine venlafaxine which is the same kind of medicine as the medicine in desvenlafaxine have had lung problems. Symptoms of lung problems include difficulty breathing, cough, or chest discomfort. Tell your healthcare provider right away if you have any of these symptoms.
Common side effects with desvenlafaxine include:

• nausea

• dizziness

• insomnia

• sweating

• constipation

• sleepiness

• loss of appetite

• anxiety

• decreased sex drive

• delayed orgasm and ejaculation

These are not all the possible side effects of desvenlafaxine. Tell your healthcare provider about any side effect that bothers you or does not go away.
Call your doctor for medical advice about side effects. You may report side effects to FDA at 1-800-FDA-1088.
How should I store desvenlafaxine?
• Store desvenlafaxine at room temperature between 68°F to 77°F (20°C to 25°C).
• Do not use desvenlafaxine after the expiration date (EXP), which is on the container. The expiration date refers to the last day of that month.
• Keep desvenlafaxine and all medicines out of the reach of children.
General Information about the safe and effective use of desvenlafaxine
Medicines are sometimes used for conditions that are not mentioned in Medication Guides. Do not use desvenlafaxine for a condition for which it was not prescribed. Do not give desvenlafaxine to other people, even if they have the same symptoms that you have. It may harm them.
This Medication Guide summarizes the most important information about desvenlafaxine. If you would like more information, talk with your healthcare provider. You can ask your pharmacist or healthcare provider for information about desvenlafaxine that is written for healthcare professionals.
What are the ingredients in desvenlafaxine extended-release tablets?
Active ingredient: desvenlafaxine
Inactive ingredients: For the 50 mg tablet, alginic acid, citric acid monohydrate powder, hypromellose, microcrystalline cellulose, povidone, talc, magnesium stearate and film coating, which consist of hypromellose, titanium dioxide, polyethylene glycol, talc, and iron oxide red.
For the 100 mg tablet, alginic acid, citric acid monohydrate powder, hypromellose, microcrystalline cellulose, povidone, talc, magnesium stearate and film coating, which consist of hypromellose, titanium dioxide, polyethylene glycol, iron oxide red, and iron oxide black.
This Medication Guide has been approved by the U.S. Food and Drug Administration.
Manufactured by:
Alembic Pharmaceuticals Limited
(Formulation Division),
Village Panelav, P. O. Tajpura, Near Baska,
Taluka-Halol, Panchmahal, Gujarat, India.
Revised: 09/2019

PACKAGE LABEL.PRINCIPAL DISPLAY PANEL- 50 mg

NDC 46708-152-30
Desvenlafaxine
Extended-Release Tablets
50 mg
PHARMACIST: Dispense the accompanying
Medication Guide to each patient.
Rx only
30 Tablets
Alembic

PACKAGE LABEL.PRINCIPAL DISPLAY PANEL- 100 mg

NDC 46708-153-30
Desvenlafaxine
Extended-Release Tablets
100 mg
PHARMACIST: Dispense the accompanying
Medication Guide to each patient.
Rx only
30 Tablets
Alembic